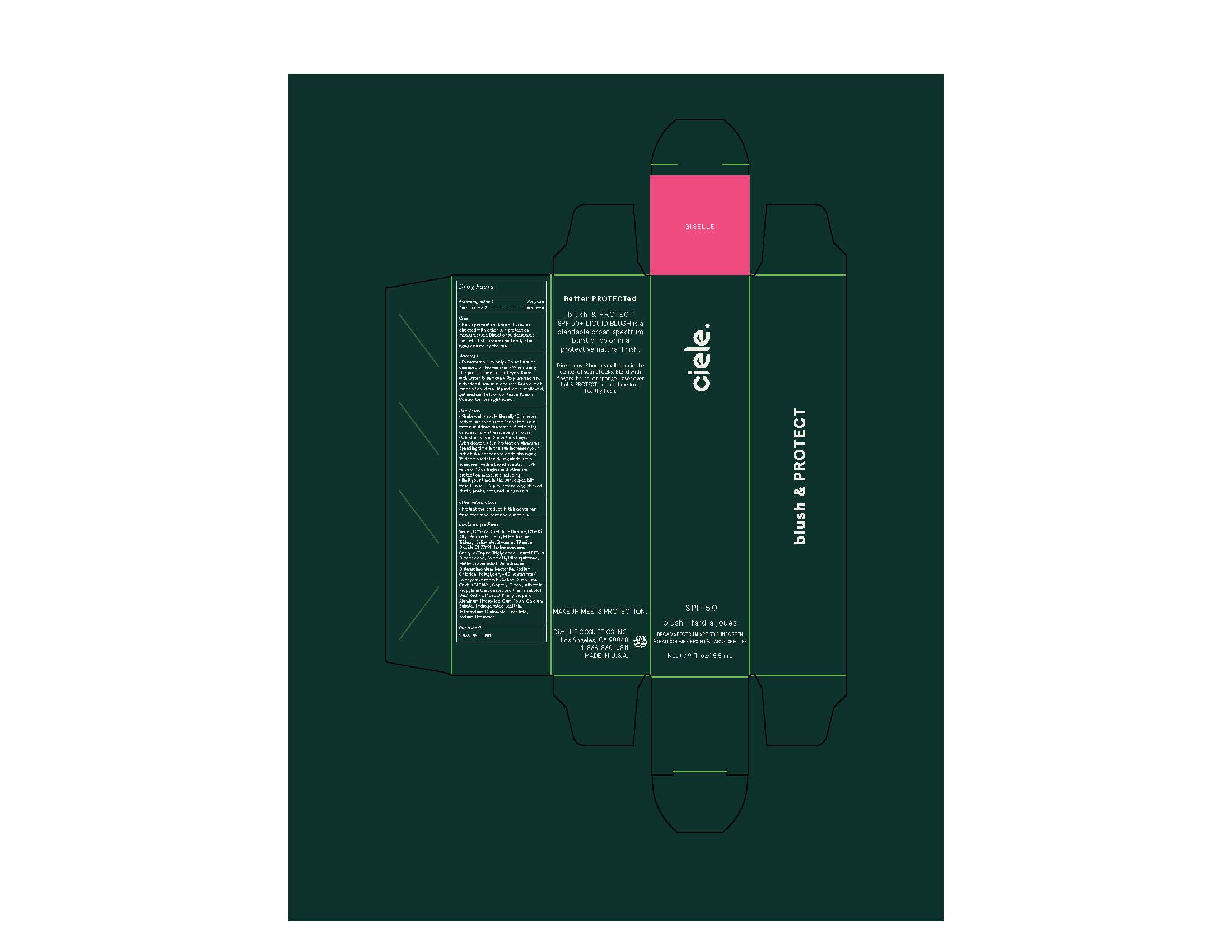 DRUG LABEL: Ciele Blush and Protect
NDC: 83103-1513 | Form: LOTION
Manufacturer: Ciele
Category: otc | Type: HUMAN OTC DRUG LABEL
Date: 20251015

ACTIVE INGREDIENTS: ZINC OXIDE 73.6 mg/1 mL
INACTIVE INGREDIENTS: TITANIUM DIOXIDE; FERRIC OXIDE RED; LECITHIN, SOYBEAN; PHENYLPROPANOL; ALLANTOIN; SODIUM SULFATE; LAURYL PEG-8 DIMETHICONE (300 CPS); ISOHEXADECANE; DISTEARDIMONIUM HECTORITE; TRIDECYL SALICYLATE; SODIUM HYDROXIDE; WATER; TETRASODIUM GLUTAMATE DIACETATE; SODIUM CHLORIDE; ALKYL (C12-15) BENZOATE; SILICON DIOXIDE; POLYMETHYLSILSESQUIOXANE (11 MICRONS); .ALPHA.-BISABOLOL, (+)-; GLYCERIN; METHYLPROPANEDIOL; DIMETHICONE; ALUMINUM HYDROXIDE; POLYGLYCERYL-4 DIISOSTEARATE/POLYHYDROXYSTEARATE/SEBACATE; PROPYLENE CARBONATE; FERRIC OXIDE YELLOW; CAPRYLYL GLYCOL

Ciele Blush and Protect